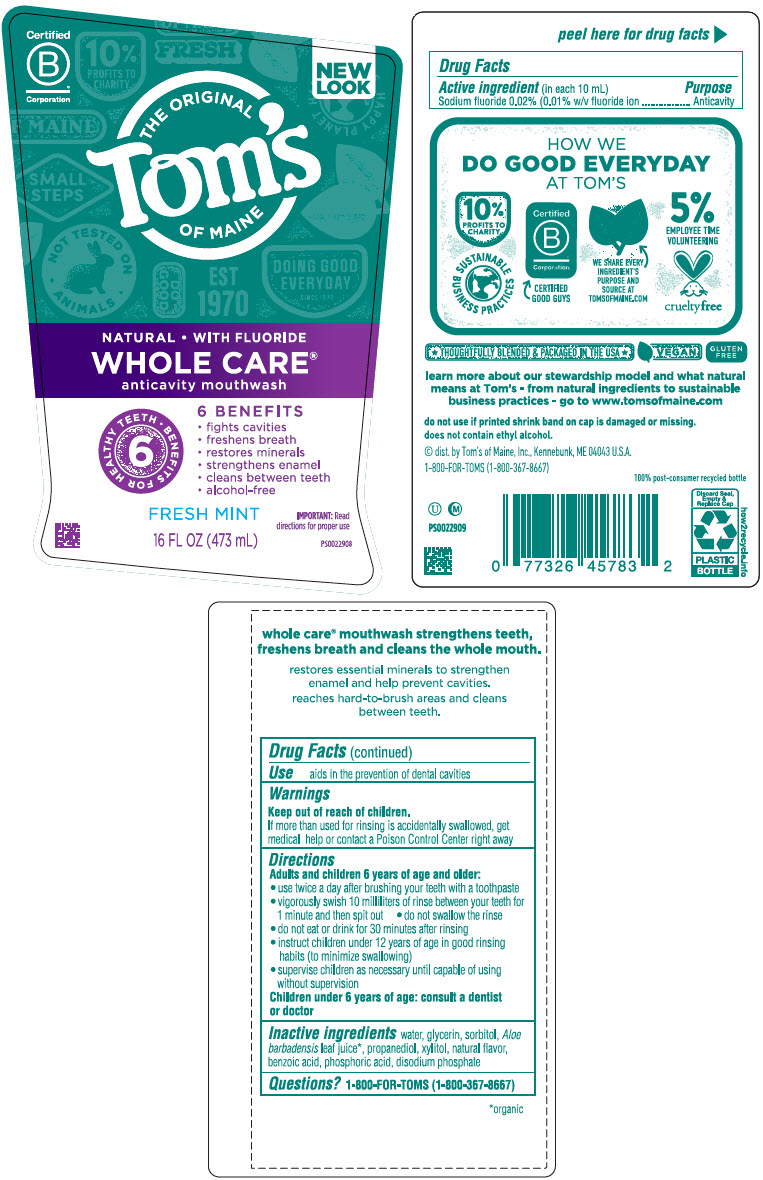 DRUG LABEL: Toms Whole Care Mouthwash Fresh Mint
NDC: 51009-837 | Form: RINSE
Manufacturer: Tom's of Maine, Inc.
Category: otc | Type: HUMAN OTC DRUG LABEL
Date: 20240118

ACTIVE INGREDIENTS: SODIUM FLUORIDE 1 mg/10 mL
INACTIVE INGREDIENTS: WATER; GLYCERIN; PROPANEDIOL; XYLITOL; SODIUM PHOSPHATE, DIBASIC, ANHYDROUS; BENZOIC ACID; ALOE VERA LEAF; SORBITOL; PHOSPHORIC ACID

Tom's Whole Care® Mouthwash Fresh Mint

Drug Facts

Active ingredient (in each 10 mL)

Sodium fluoride 0.02% (0.01% w/v fluoride ion)

Purpose

Anticavity

Use

aids in the prevention of dental cavities

Warnings

Keep out of reach of children.

If more than used for rinsing is accidentally swallowed, get medical help or contact a Poison Control Center right away

Directions

Adults and children 6 years of age and older:

- use twice a day after brushing your teeth with a toothpaste
- vigorously swish 10 milliliters of rinse between your teeth for 1 minute and then spit out
- do not swallow the rinse
- do not eat or drink for 30 minutes after rinsing
- instruct children under 12 years of age in good rinsing habits (to minimize swallowing)
- supervise children as necessary until capable of using without supervision

Children under 6 years of age: consult a dentist or doctor

Inactive ingredients

water, glycerin, sorbitol, Aloe barbadensis leaf juice [organic] , propanediol, xylitol, natural flavor, benzoic acid, phosphoric acid, disodium phosphate

Questions?

1-800-FOR-TOMS (1-800-367-8667)

© Dist. by TOM'S OF MAINE, INC., KENNEBUNK, ME 04043 U.S.A.

PRINCIPAL DISPLAY PANEL - 473 mL Bottle Label

Certified
B®
Corporation

NEW
LOOK

THE ORIGINAL
Tom's
OF MAINE

NATURAL • WITH FLUORIDE
WHOLE CARE®
anticavity mouthwash

6 • BENEFITS FOR HEALTHY TEETH

6 BENEFITS

- fights cavities
- freshens breath
- restores minerals
- strengthens enamel
- cleans between teeth
- alcohol-free

FRESH MINT

16 FL OZ (473 mL)

IMPORTANT: Read
directions for proper use

PS0022908